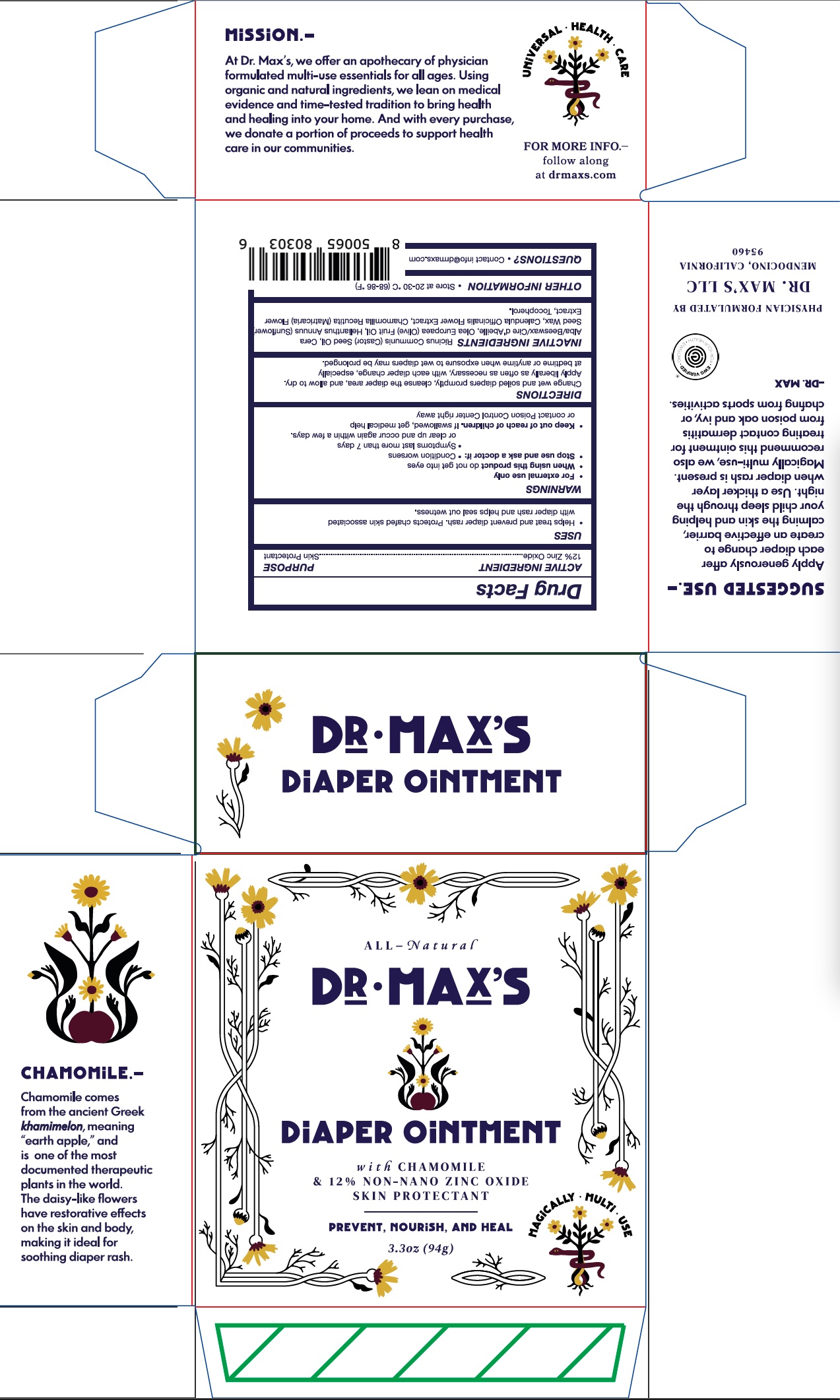 DRUG LABEL: Dr. Maxs Diaper
NDC: 85453-101 | Form: OINTMENT
Manufacturer: Dr. Max’s LLC
Category: otc | Type: HUMAN OTC DRUG LABEL
Date: 20250401

ACTIVE INGREDIENTS: ZINC OXIDE 12 g/100 g
INACTIVE INGREDIENTS: CALENDULA OFFICINALIS FLOWER; TOCOPHEROL; CHAMOMILE; BEESWAX; RICINUS COMMUNIS (CASTOR) SEED OIL; OLEA EUROPAEA (OLIVE) FRUIT OIL; HELIANTHUS ANNUUS (SUNFLOWER) SEED WAX

Dr. Max's Diaper Ointment (85453-101)

ACTIVE INGREDIENTS

ZINC OXIDE 12%

PURPOSE

Skin Protectant

USES

Helps treat and prevent diaper rash. Protects chafed skin associated with diaper rash and helps seal out wetness.

WARNINGS

For external use only.

When using this product do not get into eyes.

Stop use and ask a doctor if: Condition worsens. Symptoms last more than 7 days or clear up and occur again within a few days.

Keep out of reach of children. If swallowed, get medical help or contact poison control right away.

DIRECTIONS

Change wet and soiled diapers promptly, cleanse the diaper area, and allow to dry.

Apply liberally as often as necessary, with each diaper change, especially at bedtime or anytime when exposure to wet diapers maybe prolonged.

INACTIVE INGREDIENTS

Ricinus Communis (Castor) Seed Oil, Cera Alba/Beeswax/Cire d'Abeille, Olea Europaea (Olive) Fruit Oil, Helianthus Annuus (Sunflower) Seed Wax, Calendula Officinalis Flower Extract, Chamomilla Recutita (Matricaria) Flower Extract, Tocopherol.

OTHER INFORMATION

Store at 20-30 °C (68-86 °F)

QUESTIONS?

Contact info@drmaxs.com